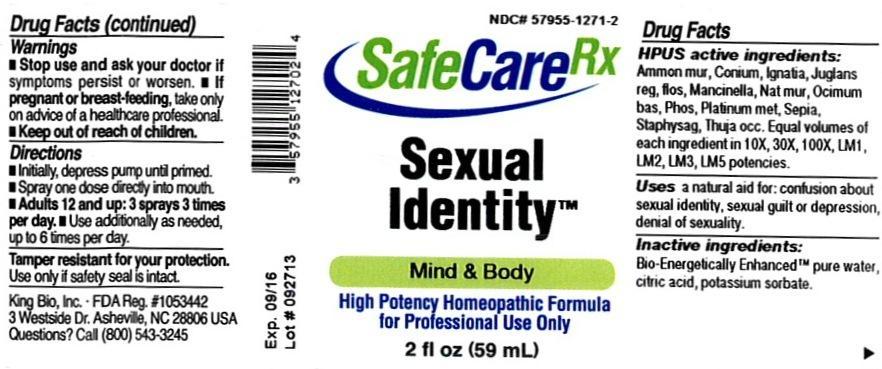 DRUG LABEL: Sexual Identity
NDC: 57955-1271 | Form: LIQUID
Manufacturer: King Bio Inc.
Category: homeopathic | Type: HUMAN OTC DRUG LABEL
Date: 20131210

ACTIVE INGREDIENTS: AMMONIUM CHLORIDE 10 [hp_X]/59 mL; CONIUM MACULATUM FLOWERING TOP 10 [hp_X]/59 mL; STRYCHNOS IGNATII SEED 10 [hp_X]/59 mL; JUGLANS REGIA FLOWERING TOP 10 [hp_X]/59 mL; HIPPOMANE MANCINELLA FRUITING LEAFY TWIG 10 [hp_X]/59 mL; SODIUM CHLORIDE 10 [hp_X]/59 mL; BASIL 10 [hp_X]/59 mL; PHOSPHORUS 10 [hp_X]/59 mL; PLATINUM 10 [hp_X]/59 mL; SEPIA OFFICINALIS JUICE 10 [hp_X]/59 mL; DELPHINIUM STAPHISAGRIA SEED 10 [hp_X]/59 mL; THUJA OCCIDENTALIS LEAFY TWIG 10 [hp_X]/59 mL
INACTIVE INGREDIENTS: WATER; CITRIC ACID MONOHYDRATE; POTASSIUM SORBATE

Sexual Identity

Drug Facts

____________________________________________________________________________________________________________________

HPUS active ingredients: Ammonium muriaticum, Conium maculatum, Ignatia amara, Juglans regia, flos, Mancinella, Natrum muriaticum, Ocimum basilicum, Phosphorus, Platinum metallicum, Sepia, Staphysagria, Thuja occidentalis. Equal volumes of each ingredient in 10X, 30X, 100X, LM1, LM2, LM3, LM5 potencies.

INDICATIONS AND USAGE

Uses a natural aid for: confusion about sexual identity, sexual guilt or depression, denial of sexuality.

INACTIVE INGREDIENT

Inactive ingredients: Bio-Energetically Enhanced pure water, citric acid, potassium sorbate.

Warnings

- Stop use and ask your doctor if symptoms persist or worsen.
- If pregnant or breast-feeding, take only on advice of a healthcare professional.

- Keep out of reach of children.

Directions:

- Initially, depress pump until primed.
- Spray one dose directly into mouth.
- Adults 12 and up: 3 sprays 3 times per day.
- Use additionally as needed, up to 6 times per day.

OTHER SAFETY INFORMATION

Tamper resistant for your protection. Use only if safety seal is intact.

PURPOSE

Uses a natural aid for:

- confusion about sexual identity
- sexual guilt or depression
- denial of sexuality.